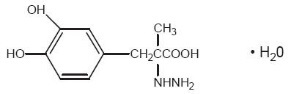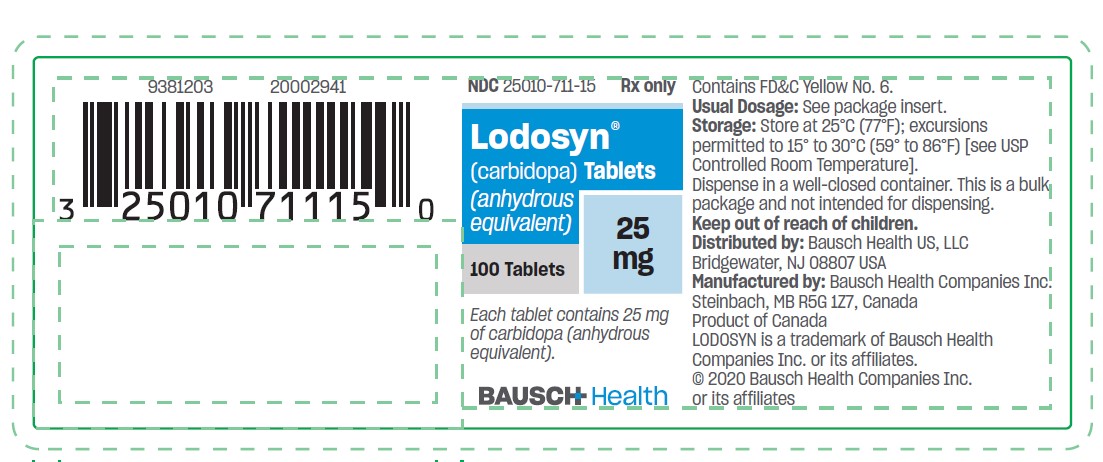 DRUG LABEL: Lodosyn
NDC: 25010-711 | Form: TABLET
Manufacturer: Bausch Health US, LLC
Category: prescription | Type: HUMAN PRESCRIPTION DRUG LABEL
Date: 20200701

ACTIVE INGREDIENTS: carbidopa 25 mg/1 1
INACTIVE INGREDIENTS: powdered cellulose; FD&C Yellow No. 6; magnesium stearate; starch, corn

LODOSYN®
(carbidopa)
Tablets

When LODOSYN (carbidopa) is to be given to carbidopa-naive patients who are being treated with levodopa, the two drugs should be given at the same time, starting with no more than 20 to 25% of the previous daily dosage of levodopa when given without LODOSYN (carbidopa). At least twelve hours should elapse between the last dose of levodopa and initiation of therapy with LODOSYN(carbidopa)and levodopa.See theWARNINGS and DOSAGE AND ADMINISTRATIONsections beforeinitiating therapy.

DESCRIPTION

Carbidopa, an inhibitor of aromatic amino acid decarboxylation, is a white, crystalline compound, slightly soluble in water, with a molecular weight of 244.3. It is designated chemically as (–)-L-α-hydrazino-α-methyl-β-(3,4-dihydroxybenzene) propanoic acid monohydrate. Its empirical formula is C10H14N2O4 •H2O, and its structural formula is:

LODOSYN (carbidopa) tablets contain 25 mg of carbidopa. Inactive ingredients are microcrystalline cellulose, FD&C Yellow No. 6, magnesium stearate and pregelatinized starch.

Tablet content is expressed in terms of anhydrous carbidopa which has a molecular weight of 226.3.

CLINICAL PHARMACOLOGY

Parkinson’s disease is a progressive, neurodegenerative disorder of the extrapyramidal nervous system affecting the mobility and control of the skeletal muscular system. Its characteristic features include resting tremor, rigidity, and bradykinetic movements. Symptomatic treatments, such as levodopa therapies, may permit the patient better mobility.

Mechanism of Action

Current evidence indicates that symptoms of Parkinson’s disease are related to depletion of dopamine in the corpus striatum. Administration of dopamine is ineffective in the treatment of Parkinson’s disease apparently because it does not cross the blood-brain barrier. However, levodopa, the metabolic precursor of dopamine, does cross the blood-brain barrier, and presumably is converted to dopamine in the brain. This is thought to be the mechanism whereby levodopa relieves symptoms of Parkinson’s disease.

Pharmacodynamics

When levodopa is administered orally it is rapidly decarboxylated to dopamine in extracerebral tissues so that only a small portion of a given dose is transported unchanged to the central nervous system. For this reason, large doses of levodopa are required for adequate therapeutic effect and these may often be accompanied by nausea and other adverse reactions, some of which are attributable to dopamine formed in extracerebral tissues.

The incidence of levodopa-induced nausea and vomiting is less when LODOSYN is used with levodopa than when levodopa is used without LODOSYN. In many patients this reduction in nausea and vomiting will permit more rapid dosage titration.

Carbidopa inhibits decarboxylation of peripheral levodopa. Carbidopa has not been demonstrated to have any overt pharmacodynamic actions in the recommended doses. It does not appear to cross the blood-brain barrier readily and does not affect the metabolism of levodopa within the central nervous system at doses of carbidopa that are recommended for maximum effective inhibition of peripheral decarboxylation of levodopa.

Since its decarboxylase-inhibiting activity is limited primarily to extracerebral tissues, administration of carbidopa with levodopa makes more levodopa available for transport to the brain. However, since levodopa and carbidopa compete with certain amino acids for transport across the gut wall, the absorption of levodopa and carbidopa may be impaired in some patients on a high protein diet.

Pharmacokinetics

Carbidopa reduces the amount of levodopa required to produce a given response by about 75% and, when administered with levodopa, increases both plasma levels and the plasma half-life of levodopa, and decreases plasma and urinary dopamine and homovanillic acid.

In clinical pharmacologic studies, simultaneous administration of separate tablets of carbidopa and levodopa produced greater urinary excretion of levodopa in proportion to the excretion of dopamine when compared to the two drugs administered at separate times.

Supplemental pyridoxine (vitamin B6) can be given to patients when they are receiving LODOSYN and levodopa concomitantly or the fixed combination carbidopa-levodopa or carbidopa-levodopa extended release. Previous reports in the medical literature cautioned that high doses of vitamin B6 should not be taken by patients on levodopa therapy alone because exogenously administered pyridoxine would enhance the metabolism of levodopa to dopamine. The introduction of carbidopa to levodopa therapy, which inhibits the peripheral decarboxylation of levodopa to dopamine, counteracts the metabolic-enhancing effect of pyridoxine.

Carbidopa is combined with levodopa in carbidopa-levodopa and carbidopa-levodopa extended release tablets.

INDICATIONS AND USAGE

LODOSYN is indicated for use with carbidopa-levodopa or with levodopa in the treatment of the symptoms of idiopathic Parkinson’s disease (paralysis agitans), postencephalitic parkinsonism, and symptomatic parkinsonism, which may follow injury to the nervous system by carbon monoxide intoxication and/or manganese intoxication.

LODOSYN is for use with carbidopa-levodopa in patients for whom the dosage of carbidopa-levodopa provides less than adequate daily dosage (usually 70 mg daily) of carbidopa.

LODOSYN is for use with levodopa in the occasional patient whose dosage requirement of carbidopa and levodopa necessitates separate titration of each medication.

LODOSYN is used with carbidopa-levodopa or with levodopa to permit the administration of lower doses of levodopa with reduced nausea and vomiting, more rapid dosage titration, and with a somewhat smoother response. However, patients with markedly irregular (“on-off”) responses to levodopa have not been shown to benefit from the addition of carbidopa.

Since carbidopa prevents the reversal of levodopa effects caused by pyridoxine, supplemental pyridoxine (vitamin B6), can be given to patients when they are receiving carbidopa and levodopa concomitantly or as carbidopa-levodopa.

Although the administration of LODOSYN permits control of parkinsonism and Parkinson’s disease with much lower doses of levodopa, there is no conclusive evidence at present that this is beneficial other than in reducing nausea and vomiting, permitting more rapid titration, and providing a somewhat smoother response to levodopa.

Certain patients who responded poorly to levodopa alone have improved when carbidopa and levodopa were given concurrently. This was most likely due to decreased peripheral decarboxylation of levodopa rather than to a primary effect of carbidopa on the peripheral nervous system. Carbidopa has not been shown to enhance the intrinsic efficacy of levodopa.

In deciding whether to give LODOSYN with carbidopa-levodopa or with levodopa to patients who have nausea and/or vomiting, the physician should be aware that, while many patients may be expected to improve, some may not. Since one cannot predict which patients are likely to improve, this can only be determined by a trial of therapy. It should be further noted that in controlled trials comparing carbidopa and levodopa with levodopa alone, about half the patients with nausea and/or vomiting on levodopa alone improved spontaneously despite being retained on the same dose of levodopa during the controlled portion of the trial.

CONTRAINDICATIONS

LODOSYN is contraindicated in patients with known hypersensitivity to any component of this drug.

Nonselective monoamine oxidase (MAO) inhibitors are contraindicated for use with levodopa or carbidopa-levodopa combination products with or without LODOSYN. These inhibitors must be discontinued at least two weeks prior to initiating therapy with levodopa. Carbidopa-levodopa, or levodopa may be administered concomitantly with the manufacturer’s recommended dose of an MAO inhibitor with selectivity for MAO type B (e.g., selegiline HCl) (see PRECAUTIONS, Drug Interactions).

Levodopa or carbidopa-levodopa products, with or without LODOSYN, are contraindicated in patients with narrow-angle glaucoma.

WARNINGS

LODOSYN (carbidopa) has no antiparkinsonian effect when given alone. It is indicated for use with carbidopa-levodopa or levodopa. LODOSYN (carbidopa) does not decrease adverse reactions due to central effects of levodopa.

When LODOSYN (carbidopa) is to be given to carbidopa-naive patients who are being treated with levodopa alone, the two drugs should be given at the same time. At least twelve hours should elapse between the last dose of levodopa and initiation of therapy with LODOSYN (carbidopa) and levodopa in combination. Start with no more than one-fifth (20%) to one-fourth (25%) of the previous daily dosage of levodopa when given without LODOSYN (carbidopa). See theDOSAGE AND ADMINISTRATIONsection before initiating therapy.

The addition of LODOSYN with levodopa or carbidopa-levodopa reduces the peripheral effects (nausea, vomiting) due to decarboxylation of levodopa; however, LODOSYN does not decrease the adverse reactions due to the central effects of levodopa. Because LODOSYN permits more levodopa to reach the brain and more dopamine to be formed, certain adverse central nervous system (CNS) effects, e.g., dyskinesias (involuntary movements), may occur at lower dosages and sooner with levodopa in combination with LODOSYN than with levodopa alone.

Falling Asleep During Activities of Daily Living and Somnolence
Patients taking carbidopa-levodopa products alone or with other dopaminergic drugs have reported suddenly falling asleep without prior warning of sleepiness while engaged in activities of daily living (includes operation of motor vehicles). Some of these episodes resulted in automobile accidents. Although many of these patients reported somnolence while on dopaminergic medications, some did perceive that they had no warning signs, such as excessive drowsiness, and believed that they were alert immediately prior to the event. Some patients reported these events one year after the initiation of treatment.

Falling asleep while engaged in activities of daily living usually occurs in patients experiencing pre-existing somnolence, although some patients may not give such a history. For this reason, prescribers should continually reassess patients for drowsiness or sleepiness especially since some of the events occur after the start of treatment. Prescribers should be aware that patients may not acknowledge drowsiness or sleepiness until directly questioned about drowsiness or sleepiness during specific activities. Patients who have already experienced somnolence or an episode of sudden sleep onset should not participate in these activities during treatment with LODOSYN when taking it with other carbidopa-levodopa products.

Before initiating treatment with LODOSYN, advise patients about the potential to develop drowsiness and ask specifically about factors that may increase the risk for somnolence with LODOSYN such as the use of concomitant sedating medications and the presence of sleep disorders. Consider discontinuing LODOSYN in patients who report significant daytime sleepiness or episodes of falling asleep during activities that require active participation (e.g., conversations, eating, etc.). If treatment with LODOSYN continues, patients should be advised not to drive and to avoid other potentially dangerous activities that might result in harm if the patients become somnolent. There is insufficient information to establish that dose reduction will eliminate episodes of falling asleep while engaged in activities of daily living.

Hyperpyrexia and Confusion

Sporadic cases of a symptom complex resembling neuroleptic malignant syndrome (NMS) have been reported in association with dose reductions or withdrawal of certain antiparkinsonian agents such as levodopa, carbidopa-levodopa, or carbidopa-levodopa extended release. Therefore, patients should be observed carefully when the dosage of levodopa or carbidopa-levodopa is reduced abruptly or discontinued, especially if the patient is receiving neuroleptics.

NMS is an uncommon but life-threatening syndrome characterized by fever or hyperthermia. Neurological findings, including muscle rigidity, involuntary movements, altered consciousness, mental status changes; other disturbances, such as autonomic dysfunction, tachycardia, tachypnea, sweating, hyper- or hypotension; laboratory findings, such as creatine phosphokinase elevation, leukocytosis, myoglobinuria, and increased serum myoglobin, have been reported.

The early diagnosis of this condition is important for the appropriate management of these patients. Considering NMS as a possible diagnosis and ruling out other acute illnesses (e.g., pneumonia, systemic infection, etc.) is essential. This may be especially complex if the clinical presentation includes both serious medical illness and untreated or inadequately treated extrapyramidal signs and symptoms (EPS). Other important considerations in the differential diagnosis include central anticholinergic toxicity, heat stroke, drug fever, and primary central nervous system (CNS) pathology.

The management of NMS should include: 1) intensive symptomatic treatment and medical monitoring and 2) treatment of any concomitant serious medical problems for which specific treatments are available. Dopamine agonists, such as bromocriptine, and muscle relaxants, such as dantrolene, are often used in the treatment of NMS; however, their effectiveness has not been demonstrated in controlled studies.

PRECAUTIONS

General

As with levodopa alone, periodic evaluations of hepatic, hematopoietic, cardiovascular, and renal function are recommended during extended concomitant therapy with LODOSYN and levodopa, or with LODOSYN and carbidopa-levodopa, or any combination of these drugs.

Impulse Control/Compulsive Behaviors

Postmarketing reports suggest that patients treated with anti-Parkinson medications can experience intense urges to gamble, increased sexual urges, intense urges to spend money uncontrollably, binge eating, and other intense urges. Patients may be unable to control these urges while taking one or more of the medications that are used for the treatment of Parkinson’s disease and that increase central dopaminergic tone, including LODOSYN taken with levodopa and carbidopa. In some cases, although not all, these urges were reported to have stopped when the dose of anti-Parkinson medications was reduced or discontinued. Because patients may not recognize these behaviors as abnormal it is important for prescribers to specifically ask patients or their caregivers about the development of new or increased gambling urges, sexual urges, uncontrolled spending or other urges while being treated with LODOSYN. Physicians should consider dose reduction or stopping LODOSYN or levodopa if a patient develops such urges while taking LODOSYN with carbidopa/levodopa.

Hallucinations/Psychotic-Like Behavior

Hallucinations and psychotic-like behavior have been reported with dopaminergic medications. In general, hallucinations present shortly after the initiation of therapy and may be responsive to dose reduction in levodopa. Hallucinations may be accompanied by confusion and to a lesser extent sleep disorder (insomnia) and excessive dreaming. LODOSYN when taken with carbidopa-levodopa may have similar effects on thinking and behavior. This abnormal thinking and behavior may present with one or more symptoms, including paranoid ideation, delusions, hallucinations, confusion, psychotic-like behavior, disorientation, aggressive behavior, agitation, and delirium.

Ordinarily, patients with a major psychotic disorder should not be treated with LODOSYN and carbidopa-levodopa, because of the risk of exacerbating psychosis. In addition, certain medications used to treat psychosis may exacerbate the symptoms of Parkinson’s disease and may decrease the effectiveness of LODOSYN.

Dyskinesia

LODOSYN (carbidopa) may potentiate the dopaminergic side effects of levodopa and may cause or exacerbate preexisting dyskinesia.

Depression

Patients treated with LODOSYN and carbidopa-levodopa should be observed carefully for the development of depression with concomitant suicidal tendencies.

Melanoma

Epidemiological studies have shown that patients with Parkinson’s disease have a higher risk (2- to approximately 6-fold higher) of developing melanoma than the general population. Whether the observed increased risk was due to Parkinson’s disease or other factors, such as drugs used to treat Parkinson’s disease, is unclear.

For the reasons stated above, patients and providers are advised to monitor for melanomas frequently and on a regular basis when using LODOSYN tablets for Parkinson’s disease. Ideally, periodic skin examinations should be performed by appropriately qualified individuals (e.g., dermatologists).

Information for Patients

It is important that LODOSYN with levodopa be taken at regular intervals according to the schedule outlined by the health care provider. Caution patients not to change the prescribed dosage regimen and not to add any additional antiparkinson medications, including other carbidopa-levodopa preparations without first consulting a physician.

Advise patients that sometimes a “wearing-off” effect may occur at the end of the dosing interval. Tell patients to notify the prescriber if such response poses a problem to lifestyle. Patients should be advised that occasionally dark color (red, brown, or black) may appear in saliva, urine, or sweat after ingestion of LODOSYN and levodopa. Although the color appears to be clinically insignificant, garments may become discolored.

The patient should be advised that a change in diet to foods that are high in protein may delay the absorption of levodopa and may reduce the amount taken up in the circulation. Excessive acidity also delays stomach emptying thus delaying the absorption of levodopa. Iron salts (such as in multivitamin tablets) may also reduce the amount of levodopa available in the body. The above factors may reduce the clinical effectiveness of the LODOSYN and levodopa therapy.

Alert patients to the possibility of sudden onset of sleep during daily activities, in some cases without awareness or warning signs, when they are taking dopaminergic agents, including levodopa. Advise patients to exercise caution while driving or operating machinery and that if they have experienced somnolence and/or sudden sleep onset, they must refrain from these activities. (See WARNINGS, Falling Asleep During Activities of Daily Living and Somnolence.)

There have been reports of patients experiencing intense urges to gamble, increased sexual urges, and other intense urges, and the inability to control these urges while taking one or more of the medications that increase central dopaminergic tone and that are generally used for the treatment of Parkinson’s disease, including LODOSYN and levodopa. Although it is not proven that the medications caused these events, these urges were reported to have stopped in some cases when the dose was reduced or the medication was stopped. Prescribers should ask patients about the development of new or increased gambling urges, sexual urges, or other intense urges while taking LODOSYN and levodopa. Physicians should consider dose reduction or stopping LODOSYN if a patient develops such urges while taking LODOSYN with carbidopa/levodopa. (See PRECAUTIONS, Impulse Control/Compulsive Behaviors.)

Laboratory Tests

Abnormalities in laboratory tests may include elevations of liver function tests such as alkaline phosphatase, SGOT (AST), SGPT (ALT), lactic dehydrogenase, and bilirubin. Abnormalities in blood urea nitrogen and positive Coombs test have also been reported. Commonly, levels of blood urea nitrogen, creatinine, and uric acid are lower during concomitant administration of carbidopa and levodopa than with levodopa alone.

Levodopa and carbidopa-levodopa combination products may cause a false-positive reaction for urinary ketone bodies when a test tape is used for determination of ketonuria. This reaction will not be altered by boiling the urine specimen. False-negative tests may result with the use of glucose-oxidase methods of testing for glucosuria.

Drug Interactions

Caution should be exercised when the following drugs are administered concomitantly with LODOSYN (carbidopa) given with levodopa or carbidopa-levodopa fixed dose combination products.

Symptomatic postural hypotension has occurred when LODOSYN, given with levodopa or carbidopa-levodopa combination products, was added to the treatment of a patient receiving antihypertensive drugs. Therefore, when therapy with LODOSYN, given with or without levodopa or carbidopa-levodopa combination products, is started, dosage adjustment of the antihypertensive drug may be required.

For patients receiving monoamine oxidase inhibitors (Type A or B), (see CONTRAINDICATIONS). Concomitant therapy with selegiline or rasigiline and LODOSYN and carbidopa-levodopa may be associated with severe orthostatic hypotension not attributable to carbidopa-levodopa alone (see CONTRAINDICATIONS).

There have been rare reports of adverse reactions, including hypertension and dyskinesia, resulting from the concomitant use of tricyclic antidepressants and carbidopa-levodopa preparations.

Dopamine D2 receptor antagonists (e.g., phenothiazines, butyrophenones, risperidone) and isoniazid may reduce the therapeutic effects of levodopa. In addition, the beneficial effects of levodopa in Parkinson’s disease have been reported to be reversed by phenytoin and papaverine. Patients taking these drugs with LODOSYN and levodopa or carbidopa-levodopa combination products should be carefully observed for loss of therapeutic response.

LODOSYN and iron salts or multivitamins containing iron salts should be coadministered with caution. Iron salts can form chelates with levodopa and carbidopa and consequently reduce the bioavailability of carbidopa and levodopa.

Although metoclopramide may increase the bioavailability of levodopa by increasing gastric emptying, metoclopramide may also adversely affect disease control by its dopamine receptor antagonistic properties.

Carcinogenesis, Mutagenesis, Impairment of Fertility

Carcinogenesis

There were no significant differences between treated and control rats with respect to mortality or neoplasia in a 96-week study of carbidopa at oral doses of 25, 45, or 135 mg/kg/day. Combinations of carbidopa and levodopa (10-20, 10-50, 10-100 mg/kg/day) were given orally to rats for 106 weeks. No effect on mortality or incidence and type of neoplasia was seen when compared to concurrent controls.

Mutagenesis

Mutagenicity studies have not been performed with either carbidopa or the combination of carbidopa and levodopa.

Fertility

Carbidopa had no effect on the mating performance, fertility, or survival of the young when administered orally to rats at doses of 30, 60, or 120 mg/kg/day. The highest dose caused a moderate decrease in body weight gain in males.

The administration of carbidopa-levodopa at dose levels of 10-20, 10-50, or 10-100 mg/kg/day did not adversely affect the fertility of male or female rats, their reproductive performance, or the growth and survival of the young.

Pregnancy

TERATOGENIC EFFECTS

There are no adequate and well-controlled studies with LODOSYN in pregnant women. It has been reported from individual cases that levodopa crosses the human placental barrier, enters the fetus, and is metabolized. Carbidopa concentrations in fetal tissue appeared to be minimal. LODOSYN should be used during pregnancy only if the potential benefit justifies the potential risk to the fetus.

Carbidopa, at doses as high as 120 mg/kg/day, was without teratogenic effects in the mouse or rabbit. In the rabbit, but not in the mouse, carbidopa-levodopa produced visceral anomalies, similar to those seen with levodopa alone, at approximately 7 times the maximum recommended human dose. The teratogenic effect of levodopa in rabbits was unchanged by the concomitant administration of carbidopa.

Nursing Mothers

It is not known whether carbidopa is excreted in human milk. Because many drugs are excreted in human milk, and because of their potential for serious adverse reactions in nursing infants, a decision should be made whether to discontinue nursing or to discontinue the drug, taking into account the importance of the drug to the nursing woman.

Pediatric Use

Safety and effectiveness in pediatric patients have not been established, and use of the drug in patients below the age of 18 is not recommended.

Geriatric Use

Clinical studies of LODOSYN did not include sufficient numbers of subjects aged 65 and over to determine whether they respond differently from younger subjects. Other clinical experience has not identified differences in responses between the elderly and younger patients. In general, dose selection for an elderly patient should be cautious, usually starting at the low end of the dosing range, reflecting the greater frequency of decreased hepatic, renal, or cardiac function, and concomitant disease and other drug therapy.

ADVERSE REACTIONS

Carbidopa has not been demonstrated to have any overt pharmacodynamic actions in the recommended doses. The only adverse reactions that have been observed have been with concomitant use of carbidopa with other drugs such as levodopa, and with carbidopa-levodopa combination products.

When LODOSYN is administered concomitantly with levodopa or carbidopa-levodopa combination products, the most common adverse reactions have included dyskinesias such as choreiform, dystonic, and other involuntary movements, and nausea. Other adverse reactions reported with LODOSYN when administered concomitantly with levodopa alone or carbidopa-levodopa combination products were psychotic episodes including delusions, hallucinations, and paranoid ideation, depression with or without development of suicidal tendencies, and dementia. Convulsions also have occurred; however, a causal relationship with concomitant use of LODOSYN and levodopa has not been established.

The following other adverse reactions have been reported with levodopa and carbidopa-levodopa combination products. These same adverse reactions may also occur when LODOSYN is administered with these products.

Body as a Whole: abdominal pain and distress, asthenia, chest pain, fatigue.

Cardiovascular: cardiac irregularities, hypertension, myocardial infarction, hypotension including orthostatic hypotension, palpitation, phlebitis, syncope.

Gastrointestinal: anorexia, bruxism, burning sensation of the tongue, constipation, dark saliva, development of duodenal ulcer, diarrhea, dry mouth, dyspepsia, dysphagia, flatulence, gastrointestinal bleeding, gastrointestinal pain, heartburn, hiccups, sialorrhea, taste alterations, vomiting.

Hematologic: hemolytic and non-hemolytic anemia, leukopenia, thrombocytopenia, agranulocytosis.

Hypersensitivity: angioedema, urticaria, pruritus, Henoch-Schonlein purpura, bullous lesions (including pemphigus-like reactions).

Metabolic: edema, weight gain, weight loss.

Musculoskeletal: back pain, leg pain, muscle cramps, shoulder pain.

Nervous System/Psychiatric: Psychotic episodes including delusions, hallucinations and paranoid ideation, NMS (see WARNINGS), bradykinetic episodes (“on-off” phenomenon), confusion, agitation, dizziness, somnolence, dream abnormalities including nightmares, insomnia, paresthesia, headache, depression with or without development of suicidal tendencies, dementia, pathological gambling, increased libido including hypersexuality, impulse control symptoms. Convulsions also have occurred; however, a causal relationship with LODOSYN and levodopa, has not been established.

Respiratory: upper respiratory infection, dyspnea, pharyngeal pain, cough.

Skin: flushing, increased sweating, malignant melanoma (see CONTRAINDICATIONS), rash, alopecia, dark sweat.

Special Senses: oculogyric crises, diplopia, blurred vision, dilated pupils.

Urogenital: dark urine, priapism, urinary frequency, urinary incontinence, urinary retention, urinary tract infection.

Laboratory Tests: abnormalities in alkaline phosphatase, SGOT (AST), SGPT (ALT), lactic dehydrogenase, bilirubin, blood urea nitrogen (BUN), Coombs test; elevated serum glucose; decreased hemoglobin and hematocrit; decreased white blood cell count and serum potassium; increased serum creatinine and uric acid; white blood cells, bacteria and blood in the urine; protein and glucose in the urine.

Miscellaneous: bizarre breathing patterns, faintness, hoarseness, hot flashes, malaise, neuroleptic malignant syndrome, sense of stimulation.

To report SUSPECTED ADVERSE REACTIONS, contact Bausch Health US, LLC at 1-800-321-4576 or FDA at 1-800-FDA-1088 or www.fda.gov/medwatch.

OVERDOSAGE

No reports of overdose with LODOSYN have been received. Management of overdosage with carbidopa is the same as that with levodopa or carbidopa-levodopa preparations.

In the event of overdosage, general supportive measures should be employed, along with immediate gastric lavage. Intravenous fluids should be administered judiciously, and an adequate airway maintained. Electrocardiographic monitoring should be instituted and the patient carefully observed for the development of arrhythmias; if required, appropriate antiarrhythmic therapy should be given. The possibility that the patient may have taken other drugs as well as LODOSYN should be taken into consideration. To date, no experience has been reported with dialysis; hence, its value in overdosage is not known. Pyridoxine is not effective in reversing the actions of LODOSYN.

Based on studies in which high doses of levodopa and/or carbidopa were administered, a significant proportion of rats and mice given single oral doses of levodopa of approximately 1,500 to 2,000 mg/kg are expected to die. A significant proportion of infant rats of both sexes are expected to die at a dose of 800 mg/kg. A significant proportion of rats are expected to die after treatment with similar doses of carbidopa. The addition of carbidopa in a 1:10 ratio with levodopa increases the dose at which a significant proportion of mice are expected to die to 3,360 mg/kg.

DOSAGE AND ADMINISTRATION

Whether given with carbidopa-levodopa or with levodopa, the optimal daily dosage of LODOSYN must be determined by careful titration. Most patients respond to a 1:10 proportion of carbidopa and levodopa, provided the daily dosage of carbidopa is 70 mg or more a day. The maximum daily dosage of carbidopa should not exceed 200 mg, since clinical experience with larger dosages is limited. If the patient is taking carbidopa-levodopa, the amount of carbidopa in carbidopa-levodopa should be considered when calculating the total amount of LODOSYN to be administered each day.

Patients Receiving Carbidopa-Levodopa Who Require Additional Carbidopa

Some patients taking carbidopa-levodopa may not have adequate reduction in nausea and vomiting when the dosage of carbidopa is less than 70 mg a day, and the dosage of levodopa is less than 700 mg a day. When these patients are taking carbidopa-levodopa, 25 mg of LODOSYN may be given with the first dose of carbidopa-levodopa each day. Additional doses of 12.5 mg or 25 mg may be given during the day with each dose of carbidopa-levodopa. LODOSYN may be given with any dose of carbidopa-levodopa as required for optimum therapeutic response. The maximum daily dosage of carbidopa, given as LODOSYN and as carbidopa-levodopa, should not exceed 200 mg.

Patients Requiring Individual Titration of Carbidopa and Levodopa Dosage

Although carbidopa-levodopa is the most frequently used of carbidopa and levodopa administration, there may be an occasional patient who requires individually titrated doses of these two drugs. In these patients, LODOSYN (carbidopa) should be initiated at a dosage of 25 mg three or four times a day. The two drugs should be given at the same time, starting with no more than one-fifth (20%) to one-fourth (25%) of the previous or recommended daily dosage of levodopa when given without LODOSYN (carbidopa). In patients already receiving levodopa therapy, at least twelve hours should elapse between the last dose of levodopa and initiation of therapy with LODOSYN (carbidopa) and levodopa. A convenient way to initiate therapy in these patients is in the morning following a night when the patient has not taken levodopa for at least twelve hours. Health care providers who prescribe separate doses of LODOSYN and levodopa should be thoroughly familiar with the directions for use of each drug.

Dosage Adjustment

Dosage of LODOSYN may be adjusted by adding or omitting one-half or one tablet a day. Because both therapeutic and adverse responses occur more rapidly with combined therapy than when only levodopa is given, patients should be monitored closely during the dose adjustment period. Specifically, involuntary movements will occur more rapidly when LODOSYN and levodopa are given concomitantly than when levodopa is given without LODOSYN. The occurrence of involuntary movements may require dosage reduction. Blepharospasm may be a useful early sign of excess dosage in some patients.

Current evidence indicates other standard antiparkinsonian drugs may be continued while carbidopa and levodopa are being administered. However, the dosage of such other standard antiparkinsonian drugs may require adjustment.

Interruption of Therapy

Sporadic cases of hyperpyrexia and confusion have been associated with dose reductions and withdrawal of carbidopa-levodopa or carbidopa-levodopa extended release. Patients should be observed carefully if abrupt reduction or discontinuation of carbidopa-levodopa or carbidopa-levodopa extended release is required, especially if the patient is receiving neuroleptics. (See WARNINGS.)

If general anesthesia is required, therapy may be continued as long as the patient is permitted to take fluids and medication by mouth. When therapy is interrupted temporarily, the patient should be observed for symptoms resembling NMS, and the usual daily dosage may be resumed as soon as the patient is able to take medication orally.

HOW SUPPLIED

LODOSYN Tablets, 25 mg, are round, orange-colored compressed tablets that are on one side flat beveled edge, bisect, embossed “711” and embossed “LODOSYN” on the other side.

They are supplied as follows:
  NDC 25010-711-15 bottles of 100.

Storage

Store at 25°C (77°F); excursions permitted to 15° to 30°C (59° to 86°F) [see USP Controlled Room Temperature].

Distributed by:
Bausch Health US, LLC
Bridgewater, NJ 08807 USA

Manufactured by:
Bausch Health Companies Inc.
Steinbach, MB R5G 1Z7, Canada

LODOSYN is a trademark of Bausch Health Companies Inc. or its affiliates.

© 2020 Bausch Health Companies Inc. or its affiliates.
  9379202 20002942

Rev. 07/2020

PRINCIPAL DISPLAY PANEL - 25 mg Tablet Bottle Label

NDC 25010-711-15

Rx only

LODOSYN®
(carbidopa) Tablets
(anhydrous equivalent)

25 mg

100 Tablets

Each tablet contains
25 mg of carbidopa
(anhydrous equivalent).

BAUSCH Health